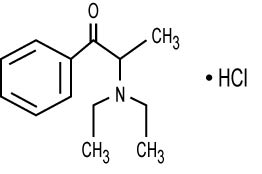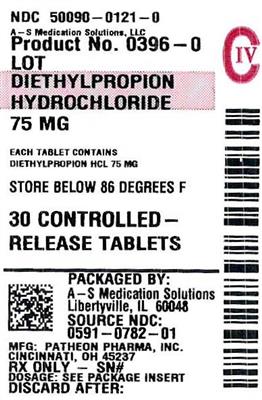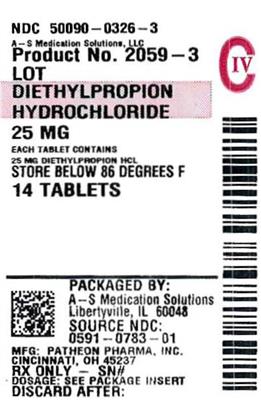 DRUG LABEL: Diethylpropion HCl Controlled-Release
NDC: 50090-0121 | Form: TABLET
Manufacturer: A-S Medication Solutions
Category: prescription | Type: HUMAN PRESCRIPTION DRUG LABEL
Date: 20181009
DEA Schedule: CIV

ACTIVE INGREDIENTS: DIETHYLPROPION HYDROCHLORIDE 75 mg/1 1
INACTIVE INGREDIENTS: CARBOMER HOMOPOLYMER TYPE B (ALLYL SUCROSE CROSSLINKED); MANNITOL; POVIDONE, UNSPECIFIED; TARTARIC ACID; ZINC STEARATE

70025263
Diethylpropion HCl USP C-IV
Immediate-Release
25 mg Tablets
Diethylpropion HCl USP C-IV
Controlled-Release
75 mg Tablets
Rx only
Rev. March 2014

DESCRIPTION

Diethylpropion hydrochloride is available for oral administration in immediate-release tablets containing 25 mg diethylpropion hydrochloride and in controlled-release tablets containing 75 mg diethylpropion hydrochloride. The inactive ingredients in each immediate-release tablet are: cornstarch, lactose, magnesium stearate, pregelatinized cornstarch, talc, and tartaric acid. The inactive ingredients in each controlled-release tablet are: carbomer 934P, mannitol, povidone, tartaric acid, zinc stearate. Diethylpropion hydrochloride is a sympathomimetic agent. The chemical name for diethylpropion hydrochloride is 1-phenyl-2-diethylamino-1-propanone hydrochloride.

Its chemical structure is:

The diethylpropion hydrochloride 75 mg formulation is dispersed in a hydrophilic matrix. On exposure to water, the diethylpropion hydrochloride is released at a relatively uniform rate as a result of slow hydration of the matrix. The result is controlled release of the anorectic agent.

CLINICAL PHARMACOLOGY

Diethylpropion hydrochloride is a sympathomimetic amine with some pharmacologic activity similar to that of the prototype drugs of this class used in obesity, the amphetamines. Actions include some central nervous system stimulation and elevation of blood pressure. Tolerance has been demonstrated with all drugs of this class in which these phenomena have been looked for.

Drugs of this class used in obesity are commonly known as "anorectics" or "anorexigenics." It has not been established, however, that the action of such drugs in treating obesity is primarily one of appetite suppression. For example, other central nervous system actions or metabolic effects may be involved. Adult obese subjects instructed in dietary management and treated with "anorectic" drugs lose more weight on the average than those treated with placebo and diet, as determined in relatively short-term clinical trials. The magnitude of increased weight loss of drug-treated patients over placebo-treated patients averages some fraction of a pound a week. However, individual weight loss may vary substantially from patient to patient. The rate of weight loss is greatest in the first weeks of therapy for both drug and placebo subjects and tends to decrease in succeeding weeks. The possible origins of the increased weight loss due to the various drug effects are not established. The amount of weight loss associated with the use of an "anorectic" drug varies from trial to trial, and the increased weight loss appears to be related in part to variables other than the drug prescribed, such as the physician/investigator relationship, the population treated, and the diet prescribed. Studies do not permit conclusions as to the relative importance of the drug and non-drug factors on weight loss.

The natural history of obesity is measured in years, whereas most studies cited are restricted to a few weeks duration; thus, the total impact of drug-induced weight loss over that of diet alone is unknown. Diethylpropion is rapidly absorbed from the GI tract after oral administration and is extensively metabolized through a complex pathway of biotransformation involving N-dealkylation and reduction. Many of these metabolites are biologically active and may participate in the therapeutic action of diethylpropion hydrochloride. Due to the varying lipid solubilities of these metabolites, their circulating levels are affected by urinary pH. Diethylpropion and/or its active metabolites are believed to cross the blood-brain barrier and the placenta.

Diethylpropion and its metabolites are excreted mainly by the kidney. It has been reported that between 75-106% of the dose is recovered in the urine within 48 hours after dosing. Using a phosphorescence assay that is specific for basic compounds containing a benzoyl group, the plasma half-life of the aminoketone metabolites is estimated to be between 4 to 6 hours.

The controlled-release characteristics of the diethylpropion hydrochloride 75 mg formulation have been demonstrated by studies in humans in which plasma levels of diethylpropion-related materials were measured by phosphorescence analysis. Plasma levels obtained with the 75 mg diethylpropion hydrochloride formulation administered once daily indicated a more gradual release than an immediate-release formulation (three 25 mg tablets given in a single dose).

The diethylpropion hydrochloride 75 mg controlled-release formulation has not been shown superior in effectiveness to the same dosage of the immediate-release formulation (one 25 mg tablet three times daily). After administration of a single dose of the diethylpropion hydrochloride 75 mg formulation (one 75 mg controlled-release tablet) or diethylpropion hydrochloride solution (75 mg dose) in a crossover study using normal human subjects, the amount of parent compound and its active metabolites recovered in the urine within 48 hours for the two dosage forms were not statistically different.

INDICATIONS AND USAGE

Diethylpropion hydrochloride is indicated in the management of exogenous obesity as a short-term adjunct (a few weeks) in a regimen of weight reduction based on caloric restriction in patients with an initial body mass index (BMI) of 30 kg/m^2 or higher and who have not responded to appropriate weight reducing regimen (diet and/or exercise) alone. Below is a chart of BMI based on various heights and weights. BMI is calculated by taking the patient’s weight, in kilograms (kg), divided by the patient’s height, in meters (m), squared. Metric conversions are as follows: pounds divided by 2.2 = kg; inches x 0.0254 = meters.

Body Mass Index (BMI), kg/m^2
Weight (pounds) | Height (feet, inches)
 | 5’0” | 5’3” | 5’6” | 5’9” | 6’0” | 6’3”
140 | 27 | 25 | 23 | 21 | 19 | 18
150 | 29 | 27 | 24 | 22 | 20 | 19
160 | 31 | 28 | 26 | 24 | 22 | 20
170 | 33 | 30 | 28 | 25 | 23 | 21
180 | 35 | 32 | 29 | 27 | 25 | 23
190 | 37 | 34 | 31 | 28 | 26 | 24
200 | 39 | 36 | 32 | 30 | 27 | 25
210 | 41 | 37 | 34 | 31 | 29 | 26
220 | 43 | 39 | 36 | 33 | 30 | 28
230 | 45 | 41 | 37 | 34 | 31 | 29
240 | 47 | 43 | 39 | 36 | 33 | 30
250 | 49 | 44 | 40 | 37 | 34 | 31

The usefulness of agents of this class (see CLINICAL PHARMACOLOGY) should be measured against possible risk factors inherent in their use such as those described below. Diethylpropion hydrochloride is indicated for use as monotherapy only.

CONTRAINDICATIONS

Pulmonary hypertension, advanced arteriosclerosis, hyperthyroidism, known hypersensitivity or idiosyncrasy to the sympathomimetic amines, glaucoma, severe hypertension. (See PRECAUTIONS.)

Agitated states.

Patients with a history of drug abuse.

Use in combination with other anorectic agents is contraindicated.

During or within 14 days following the administration of monoamine oxidase inhibitors, hypertensive crises may result.

WARNINGS

Diethylpropion hydrochloride should not be used in combination with other anorectic agents, including prescribed drugs, over-the-counter preparations, and herbal products.

In a case-control epidemiological study, the use of anorectic agents, including diethylpropion, was associated with an increased risk of developing pulmonary hypertension, a rare, but often fatal disorder. The use of anorectic agents for longer than 3 months was associated with a 23-fold increase in the risk of developing pulmonary hypertension. Increased risk of pulmonary hypertension with repeated courses of therapy cannot be excluded.

The onset or aggravation of exertional dyspnea, or unexplained symptoms of angina pectoris, syncope, or lower extremity edema suggest the possibility of occurrence of pulmonary hypertension. Under these circumstances, diethylpropion hydrochloride should be immediately discontinued, and the patient should be evaluated for the possible presence of pulmonary hypertension.

Valvular heart disease associated with the use of some anorectic agents such as fenfluramine and dexfenfluramine has been reported. Possible contributing factors include use for extended periods of time, higher than recommended dose, and/or use in combination with other anorectic drugs. Valvulopathy has been very rarely reported with diethylpropion hydrochloride monotherapy, but the causal relationship remains uncertain. The potential risk of possible serious adverse effects such as valvular heart disease and pulmonary hypertension should be assessed carefully against the potential benefit of weight loss. Baseline cardiac evaluation should be considered to detect preexisting valvular heart diseases or pulmonary hypertension prior to initiation of diethylpropion hydrochloride treatment. Diethylpropion hydrochloride is not recommended in patients with known heart murmur or valvular heart disease. Echocardiogram during and after treatment could be useful for detecting any valvular disorders which may occur.

To limit unwarranted exposure and risks, treatment with diethylpropion hydrochloride should be continued only if the patient has satisfactory weight loss within the first 4 weeks of treatment (e.g., weight loss of at least 4 pounds, or as determined by the physician and patient).

Diethylpropion hydrochloride is not recommended for patients who used any anorectic agents within the prior year.

If tolerance develops, the recommended dose should not be exceeded in an attempt to increase the effect; rather, the drug should be discontinued. Diethylpropion hydrochloride may impair the ability of the patient to engage in potentially hazardous activities such as operating machinery or driving a motor vehicle; the patient should therefore be cautioned accordingly.

Prolonged use of diethylpropion hydrochloride may induce dependence with withdrawal syndrome on cessation of therapy. Hallucinations have occurred rarely following high doses of the drug. Several cases of toxic psychosis have been reported following the excessive use of the drug and some have been reported in which the recommended dose appears not to have been exceeded. Psychosis abated after the drug was discontinued.

When central nervous system active agents are used, consideration must always be given to the possibility of adverse interactions with alcohol.

PRECAUTIONS

General

Caution is to be exercised in prescribing diethylpropion hydrochloride for patients with hypertension or with symptomatic cardiovascular disease, including arrhythmias. Diethylpropion hydrochloride should not be administered to patients with severe hypertension.

Reports suggest that diethylpropion hydrochloride may increase convulsions in some epileptics. Therefore, epileptics receiving diethylpropion hydrochloride should be carefully monitored. Titration of dose or discontinuance of diethylpropion hydrochloride may be necessary.

The least amount feasible should be prescribed or dispensed at one time in order to minimize the possibility of overdosage.

Information for Patient

The patient should be cautioned about concomitant use of alcohol or other CNS-active drugs and diethylpropion hydrochloride. (See WARNINGS.) The patient should be advised to observe caution when driving or engaging in any potentially hazardous activity.

Laboratory Tests

None.

Drug Interactions

Because diethylpropion hydrochloride is a monoamine, hypertension may result when this agent is used with monoamine oxidase (MAO) inhibitors (see CONTRAINDICATIONS).

Efficacy of diethylpropion with other anorectic agents has not been studied and the combined use may have the potential for serious cardiac problems; therefore, the concomitant use with other anorectic agents is contraindicated.

Antidiabetic drug requirements (i.e., insulin) may be altered. Concurrent use with general anesthetics may result in arrhythmias. The pressor effects of diethylpropion and those of other drugs may be additive when the drugs are used concomitantly; conversely, diethylpropion may interfere with antihypertensive drugs (i.e., guanethidine, α-methyldopa). Concurrent use of phenothiazines may antagonize the anorectic effect of diethylpropion.

Carcinogenesis, Mutagenesis, and Impairment of Fertility

No long-term animal studies have been done to evaluate diethylpropion hydrochloride for carcinogenicity. Mutagenicity studies have not been conducted. Animal reproduction studies have revealed no evidence of impairment of fertility (see Pregnancy).

Pregnancy

Teratogenic Effects

Pregnancy Category B. Reproduction studies have been performed in rats at doses up to 1.6 times the human dose (based on mg/m^2) and have revealed no evidence of impaired fertility or harm to the fetus due to diethylpropion hydrochloride. There are, however, no adequate and well-controlled studies in pregnant women. Because animal reproduction studies are not always predictive of human response, this drug should be used during pregnancy only if clearly needed.

Spontaneous reports of congenital malformations have been recorded in humans, but no causal relationship to diethylpropion has been established.

Non-teratogenic Effects

Abuse with diethylpropion hydrochloride during pregnancy may result in withdrawal symptoms in the human neonate.

Nursing Mothers

Since diethylpropion hydrochloride and/or its metabolites have been shown to be excreted in human milk, caution should be exercised when diethylpropion hydrochloride is administered to a nursing woman.

Geriatric Use

Clinical studies of diethylpropion hydrochloride did not include sufficient numbers of subjects aged 65 and over to determine whether they respond differently from younger subjects. Other reported clinical experience has not identified differences in responses between the elderly and younger patients. In general, dose selection for an elderly patient should be cautious, usually starting at the low end of the dosing range, reflecting the greater frequency of decreased hepatic, renal, or cardiac function, and of concomitant disease or other drug therapy.

This drug is known to be substantially excreted by the kidney, and the risk of toxic reactions to this drug may be greater in patients with impaired renal function. Because elderly patients are more likely to have decreased renal function, care should be taken in dose selection, and it may be useful to monitor renal function.

Pediatric Use

Since safety and effectiveness in pediatric patients below the age of 16 have not been established, diethylpropion hydrochloride is not recommended for use in pediatric patients 16 years of age and under.

ADVERSE REACTIONS

Cardiovascular: Precordial pain, arrhythmia (including ventricular), ECG changes, tachycardia, elevation of blood pressure, palpitation and rare reports of pulmonary hypertension. Valvular heart disease associated with the use of some anorectic agents such as fenfluramine and dexfenfluramine, both independently and especially when used in combination, have been reported. Valvulopathy has been very rarely reported with diethylpropion hydrochloride monotherapy, but the causal relationship remains uncertain.

Central Nervous System: In a few epileptics an increase in convulsive episodes has been reported; rarely psychotic episodes at recommended doses; dyskinesia, blurred vision, overstimulation, nervousness, restlessness, dizziness, jitteriness, insomnia, anxiety, euphoria, depression, dysphoria, tremor, mydriasis, drowsiness, malaise, headache, and cerebrovascular accident

Gastrointestinal: Vomiting, diarrhea, abdominal discomfort, dryness of the mouth, unpleasant taste, nausea, constipation, other gastrointestinal disturbances

Allergic: Urticaria, rash, ecchymosis, erythema

Endocrine: Impotence, changes in libido, gynecomastia, menstrual upset

Hematopoietic System: Bone marrow depression, agranulocytosis, leukopenia

Miscellaneous: A variety of miscellaneous adverse reactions has been reported by physicians. These include complaints such as dysuria, dyspnea, hair loss, muscle pain, increased sweating, and polyuria.

DRUG ABUSE AND DEPENDENCE

Diethylpropion hydrochloride is a schedule IV controlled substance. Diethylpropion hydrochloride has some chemical and pharmacologic similarities to the amphetamines and other related stimulant drugs that have been extensively abused. There have been reports of subjects becoming psychologically dependent on diethylpropion. The possibility of abuse should be kept in mind when evaluating the desirability of including a drug as part of a weight reduction program. Abuse of amphetamines and related drugs may be associated with varying degrees of psychologic dependence and social dysfunction which, in the case of certain drugs, may be severe. There are reports of patients who have increased the dosage to many times that recommended. Abrupt cessation following prolonged high dosage administration results in extreme fatigue and mental depression; changes are also noted on the sleep EEG. Manifestations of chronic intoxication with anorectic drugs include severe dermatoses, marked insomnia, irritability, hyperactivity, and personality changes. The most severe manifestation of chronic intoxication is psychosis, often clinically indistinguishable from schizophrenia.

OVERDOSAGE

Manifestations of acute overdosage include restlessness, tremor, hyperreflexia, rapid respiration, confusion, assaultiveness, hallucinations, panic states, and mydriasis.

Fatigue and depression usually follow the central stimulation.

Cardiovascular effects include tachycardia, arrhythmias, hypertension or hypotension and circulatory collapse. Gastrointestinal symptoms include nausea, vomiting, diarrhea, and abdominal cramps. Overdose of pharmacologically similar compounds has resulted in convulsions, coma and death.

The reported oral LD50 for mice is 600 mg/kg, for rats is 250 mg/kg and for dogs is 225 mg/kg.

Management of acute diethylpropion hydrochloride intoxication is largely symptomatic and includes lavage and sedation with a barbiturate. Experience with hemodialysis or peritoneal dialysis is inadequate to permit recommendation in this regard. Intravenous phentolamine (Regitine®) has been suggested on pharmacologic grounds for possible acute, severe hypertension, if this complicates diethylpropion hydrochloride overdosage.

DOSAGE AND ADMINISTRATION

Diethylpropion hydrochloride immediate-release:

One immediate-release 25 mg tablet three times daily, one hour before meals, and in midevening if desired to overcome night hunger.

Diethylpropion hydrochloride controlled-release:

One controlled-release 75 mg tablet daily, swallowed whole, in midmorning.

Geriatric Use:

This drug is known to be substantially excreted by the kidney, and the risk of toxic reactions to this drug may be greater in patients with impaired renal function. Because elderly patients are more likely to have decreased renal function, care should be taken in dose selection, and it may be useful to monitor renal function. (See PRECAUTIONS, Geriatric Use.)

HOW SUPPLIED

Product: 50090-0121

NDC: 50090-0121-0 30 TABLET in a BOTTLE

Product: 50090-0326

NDC: 50090-0326-4 28 TABLET in a BOTTLE

NDC: 50090-0326-5 90 TABLET in a BOTTLE

NDC: 50090-0326-7 60 TABLET in a BOTTLE

NDC: 50090-0326-8 30 TABLET in a BOTTLE

NDC: 50090-0326-3 14 TABLET in a BOTTLE